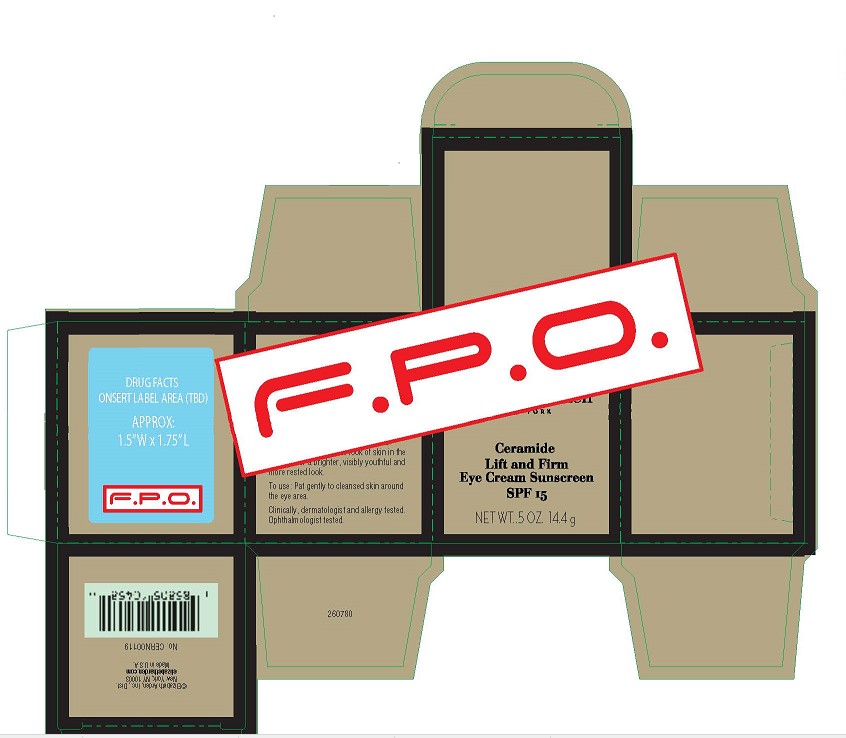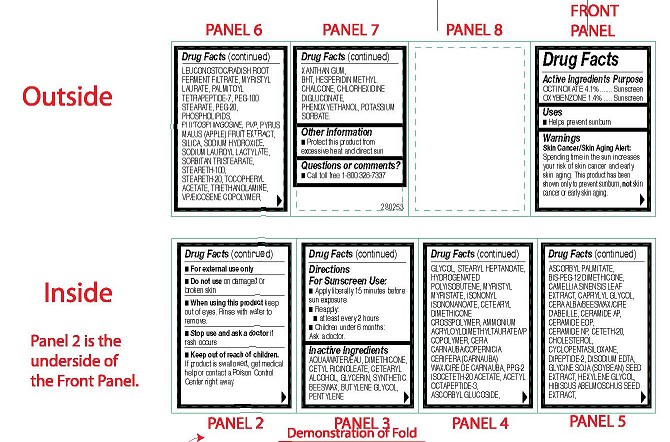 DRUG LABEL: CERAMIDE LIFT and FIRM EYE  SPF 15
NDC: 10967-667 | Form: EMULSION
Manufacturer: REVLON
Category: otc | Type: HUMAN OTC DRUG LABEL
Date: 20240112

ACTIVE INGREDIENTS: OCTINOXATE 4.1 mg/1 g; OXYBENZONE 1.4 mg/1 g
INACTIVE INGREDIENTS: SYNTHETIC BEESWAX; ISONONYL ISONONANOATE; ACETYL OCTAPEPTIDE-3; GREEN TEA LEAF; SODIUM HYDROXIDE; SODIUM LAUROYL LACTYLATE; BUTYLENE GLYCOL; CERAMIDE NP; DIMETHICONE; PPG-2 ISOCETETH-20 ACETATE; SOYBEAN; PENTYLENE GLYCOL; HYDROGENATED POLYBUTENE (1300 MW); ABELMOSCHUS MOSCHATUS SEED; BIS-PEG-12 DIMETHICONE (500 MPA.S); BUTYLATED HYDROXYTOLUENE; WATER; STEARETH-20; CHLORHEXIDINE GLUCONATE; MYRISTYL MYRISTATE; LEUCONOSTOC/RADISH ROOT FERMENT FILTRATE; STEARYL HEPTANOATE; POVIDONE, UNSPECIFIED; XANTHAN GUM; STEARETH-100; TROLAMINE; PHENOXYETHANOL; SILICON DIOXIDE; POTASSIUM SORBATE; SORBITAN TRISTEARATE; PEG-100 STEARATE; PALMITOYL TETRAPEPTIDE-7; CETYL RICINOLEATE; CETOSTEARYL ALCOHOL; GLYCERIN; CETETH-20; ASCORBYL PALMITATE; CYCLOMETHICONE 5; PHYTOSPHINGOSINE; MYRISTYL LAURATE; HEXYLENE GLYCOL; ALPHA-TOCOPHEROL ACETATE; AMMONIUM ACRYLOYLDIMETHYLTAURATE/VP COPOLYMER; CARNAUBA WAX; POLYETHYLENE GLYCOL 1000; VALYLTRYPTOPHAN; EDETATE DISODIUM ANHYDROUS; APPLE; CHOLESTEROL; VINYLPYRROLIDONE/EICOSENE COPOLYMER

CERAMIDE LIFT AND FIRM EYE CREAM SUNSCREEN SPF 15

ACTIVE INGREDIENTS PURPOSE

OCTINOXATE 4.1% ....... Sunscreen
OXYBENZONE 1.4% ....... Sunscreen

OTHER INGREDIENTS

Other Ingredients: Aqua/Water/Eau, Dimethicone, Cetyl Ricinoleate, Cetearyl Alcohol,
Glycerin, Synthetic Beeswax, Butylene Glycol, Pentylene Glycol, Stearyl Heptanoate,
Hydrogenated Polyisobutene, Myristyl Myristate, Isononyl Isononanoate, Cetearyl Dimethicone
Crosspolymer, Ammonium Acryloyldimethyltaurate/VP Copolymer, Cera Carnauba/Copernicia
Cerifera (Carnauba) Wax/Cire de carnauba, PPG-2 Isoceteth-20 Acetate, Acetyl Octapeptide-3,
Ascorbyl Glucoside, Ascorbyl Palmitate, Bis-PEG-12 Dimethicone, Camellia Sinensis Leaf
Extract, Caprylyl Glycol, Cera Alba/Beeswax/Cire D'abeille, Ceramide AP, Ceramide EOP,
Ceramide NP, Ceteth-20, Cholesterol, Cyclopentasiloxane, Dipeptide-2, Disodium EDTA,
Glycine Soja (Soybean) Seed Extract, Hexylene Glycol, Hibiscus Abelmoschus Seed Extract,
Leuconostoc/Radish Root Ferment Filtrate, Myristyl Laurate, Palmitoyl Tetrapeptide-7, PEG-100
Stearate, PEG-20, Phospholipids, Phytosphingosine, PVP, Pyrus Malus (Apple) Fruit Extract,
Silica, Sodium Hydroxide, Sodium Lauroyl Lactylate, Sorbitan Tristearate, Steareth-100,
Steareth-20, Tocopheryl Acetate, Triethanolamine, VP/Eicosene Copolymer, Xanthan Gum,
BHT, Hesperidin Methyl Chalcone, Chlorhexidine Digluconate, Phenoxyethanol, Potassium
Sorbate.

USES

- Helps prevent sunburn

WARNINGS

Skin Cancer/Skin Aging Alert:
Spending time in the sun increases your risk of skin cancer and early skin aging. This product has been shown only to prevent sunburn, not skin cancer or early skin aging.

- For external use only
- Do not use on damaged or broken skin
- When using this product keep out of eyes. Rinse with water to remove.
- Stop use and ask a doctor if rash occurs
- Keep out of reach of children.
If product is swallowed, get medical
help or contact a Poison Control
Center right away.

DIRECTIONS FOR SUNSCREEN USE

Directions
For Sunscreen Use:

- Apply liberally 15 minutes before sun exposure

- Reapply:

- at least every 2 hours
- Children under 6 months: Ask a doctor.

DOSAGE AND ADMINISTRATION

As needed

INDICATIONS AND USAGE

- Helps prevent sunburn

PURPOSE

Sunscreen

KEEP OUT OF REACH OF CHILDREN

Keep out of reach of chilren. If product is swallowed, get medical help or contact a Poison Control Center right away.